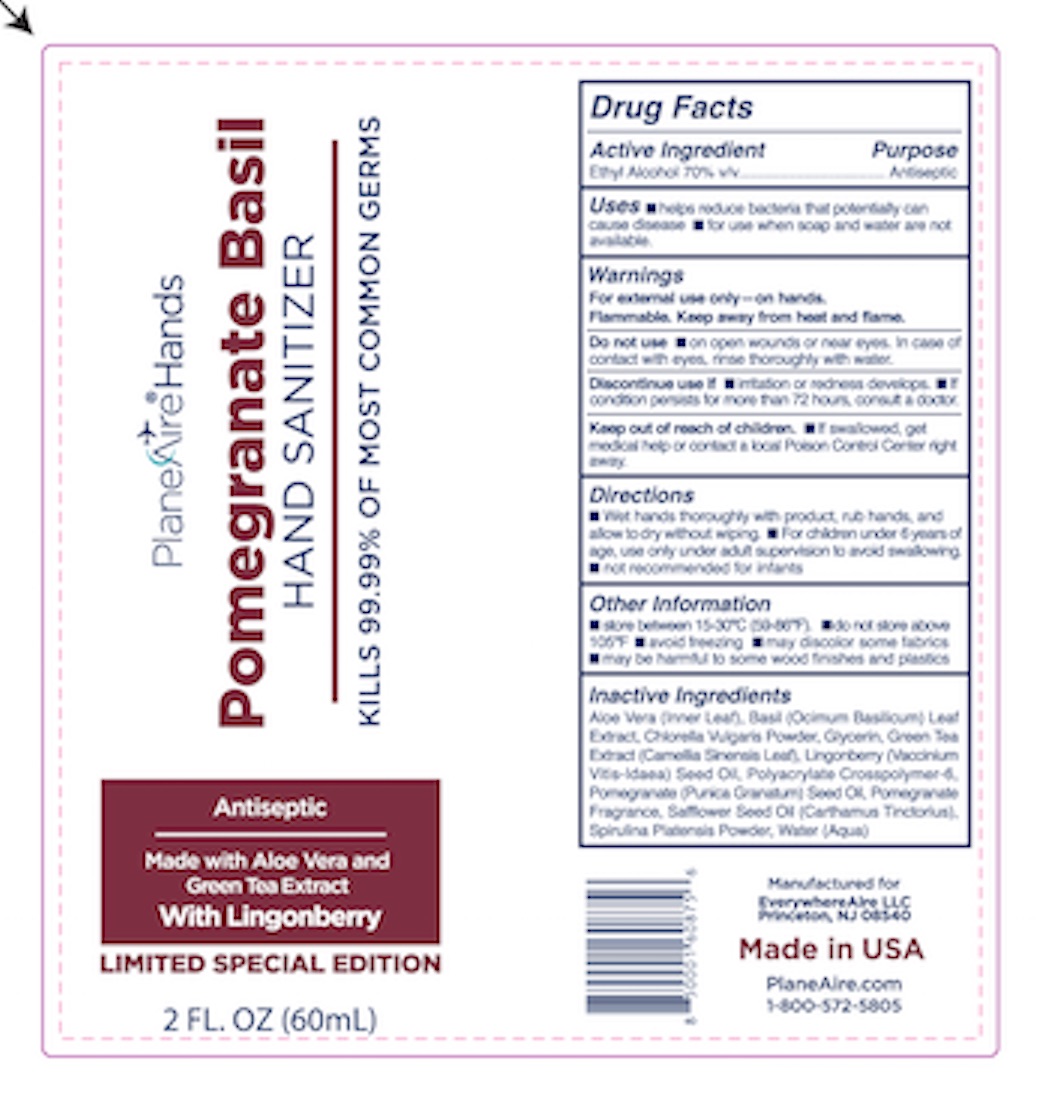 DRUG LABEL: Hand Sanitizer gel
NDC: 80335-114 | Form: GEL
Manufacturer: EverywhereAire LLC
Category: otc | Type: HUMAN OTC DRUG LABEL
Date: 20231221

ACTIVE INGREDIENTS: ALCOHOL 70 mL/100 mL
INACTIVE INGREDIENTS: CHLORELLA VULGARIS; GLYCERIN; FRAGRANCE 13576; ALOE VERA LEAF; BASIL; POMEGRANATE SEED OIL; WATER; GREEN TEA LEAF; SODIUM POLYACRYLATE (2500000 MW); SAFFLOWER OIL; LINGONBERRY SEED OIL; SPIRULINA PLATENSIS

PlaneAire Hands hand sanitizer lotion pomegranate basil lingonberry with chlorella spirulina and safflower

Active Ingredient(s)

Ethyl Alcohol 70% v/v. Purpose: Antiseptic

Purpose

Antiseptic,

Use

Helps reduce bacteria that potentially can cause disease. For use when soap and water are not available.

Warnings

For external use only- on hands. Flammable. Keep away from heat or flame

Do not use

- on open wounds or near eyes. In case of contact with eyes, rinse thoroughly with water.

WHEN USING

In case of contact with eyes, rinse eyes thoroughly with water.
Stop use if irritation or rash occurs. If condition persists for more than 72 hours, cnsukt a doctor.
Keep out of reach of children. If swallowed, get medical help or contact a Poison Control Center right away.

Stop use if irritation or rash occurs. If condition persists for more than 72 hours, consult a doctor.

Keep out of reach of children. If swallowed, get medical help or contact a local Poison Control Center right away.

Directions

- Wet hands thoroughly with product, rub hands, and allow to dry without wiping.
- For children under 6 years of age, use only under adult supervision to avoid swallowing.
- Not recommended for infants

Helps reduce bacteria that potentially can cause disease. For use when soap and water are not available.

Wet hands thoroughly with product, rub hands, and allow to dry without wiping.
For children under 6 years of age, use only under adult supervision to avoid swallowing.
Not recommended for infants

Other information

- Store between 15-30C (59-86F)
- Do not store above 105F
- Avoid freezing
- May discolor some fabrics
- May be harmful tio some wood finishes and plastics

Inactive ingredients

Aloe Vera (Inner leaf)
Basil (Ocimum Basilicum) Leaf Extract
Chlorella Vulgaris Powder
Glycerin
Green tea (Camellia Sinensis) Leaf Extract
Lingonberry (Vaccinium Vitis-Idaea) Seed Oil
Polyacrylate Crosspolymer-6
Pomegranate (Punica Granatum) seed oil
Pomegranate fragrance
Safflower (Carthamus Tinctorius) seed oil
Spirulina Platensis Powder
Water

Package Label - Principal Display Panel NDC 80335-114-02

NDC: 80335-114Pomegranate Basil hand sanitizer gel 80335-114-02